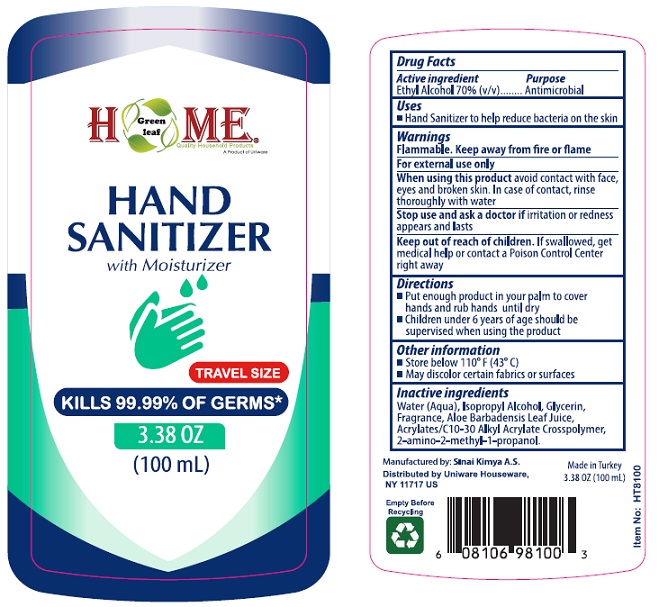 DRUG LABEL: Home Hand Sanitizer Aloe
NDC: 78712-002 | Form: GEL
Manufacturer: UNIWARE HOUSEWARE CORP.
Category: otc | Type: HUMAN OTC DRUG LABEL
Date: 20200609

ACTIVE INGREDIENTS: ALCOHOL 70 mL/100 mL
INACTIVE INGREDIENTS: WATER; ISOPROPYL ALCOHOL; GLYCERIN; CARBOMER INTERPOLYMER TYPE A (ALLYL SUCROSE CROSSLINKED); AMINOMETHYLPROPANOL; ALOE VERA LEAF

Active Ingredient

Alcohol 70% v/v.

Purpose

Antimicrobial

Uses

Hand Sanitizer to help reduce bacteria on the skin.

Warnings

Flammable. Keep away from fire or flame.

For external use only.

When using this product avoid contact with face, eyes and broken skin. In case of contact, rinse thoroughly with water.

Stop use and ask a doctor if irritation or redness appears and lasts.

Keep out of reach of children. If swallowed, get medical help or contact a Poison Control Center right away.

Directions

- Put enough product in your palm to cover hands and rub hands until dry.
- Children under 6 years of age should be supervised when using the product.

Other information

- Store below 110° F (43° C).
- May discolor certain fabrics or surfaces.

Inactive ingredients

Water (Aqua), Isopropyl Alcohol, Glycerin, Fragrance, Aloe Barbadensis Leaf Juice, Acrylates/C10-30 Alkyl Acrylate Crosspolymer, 2-amino-2-methyl-1-propanol.